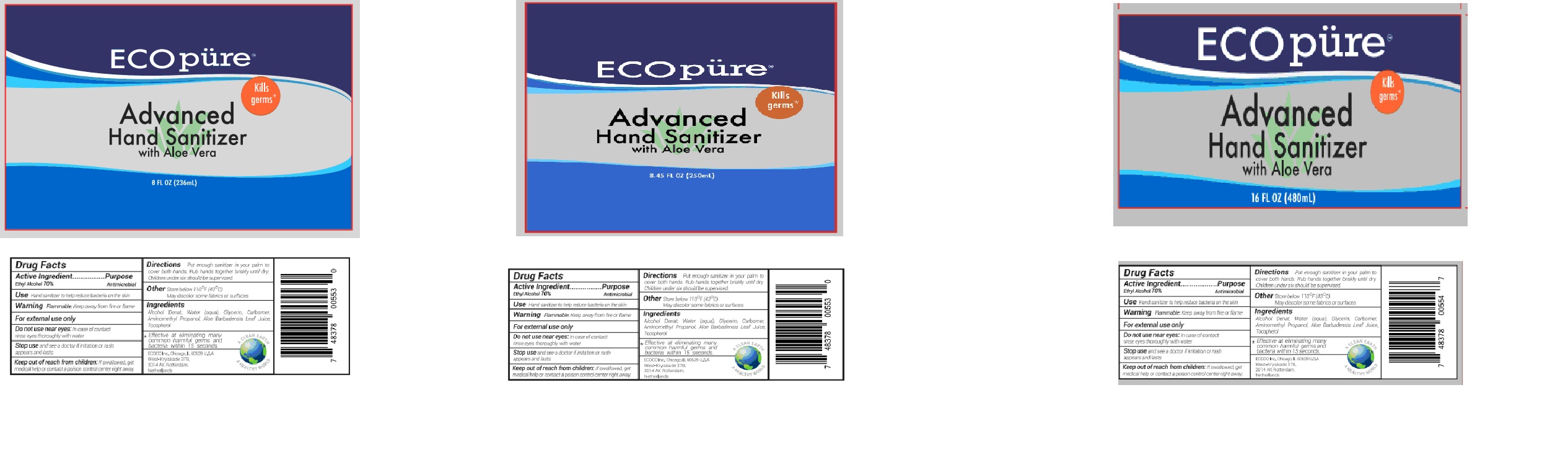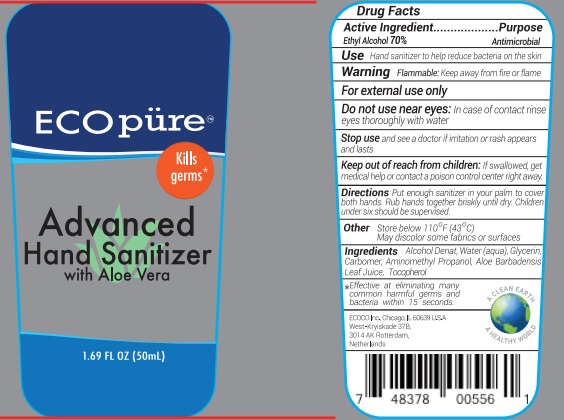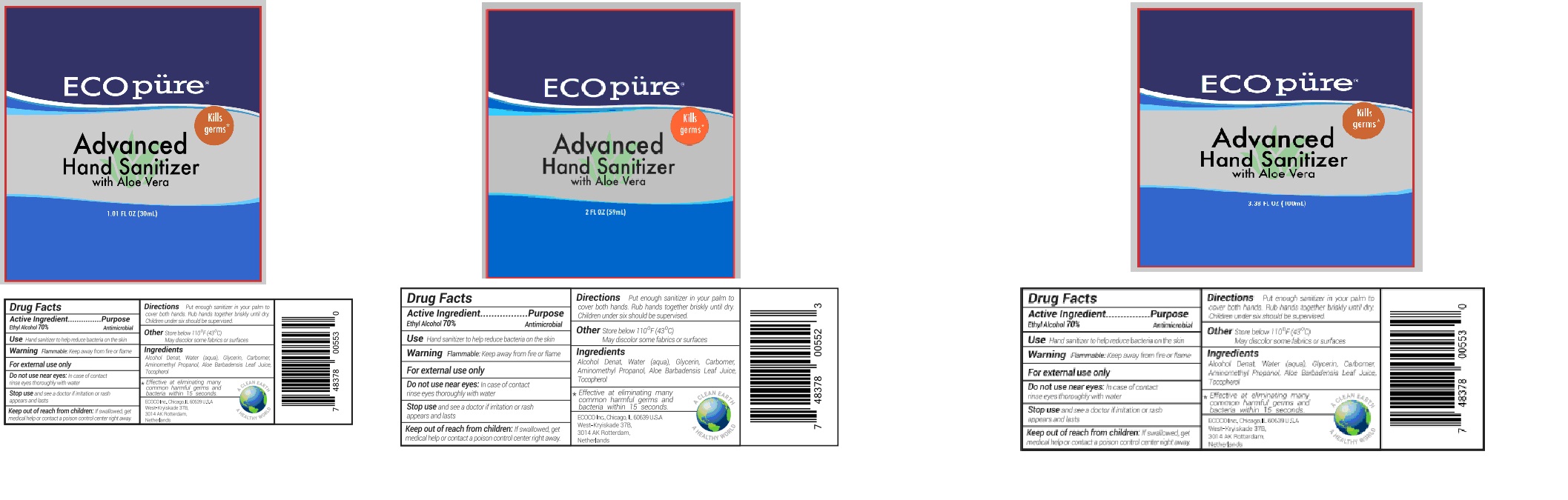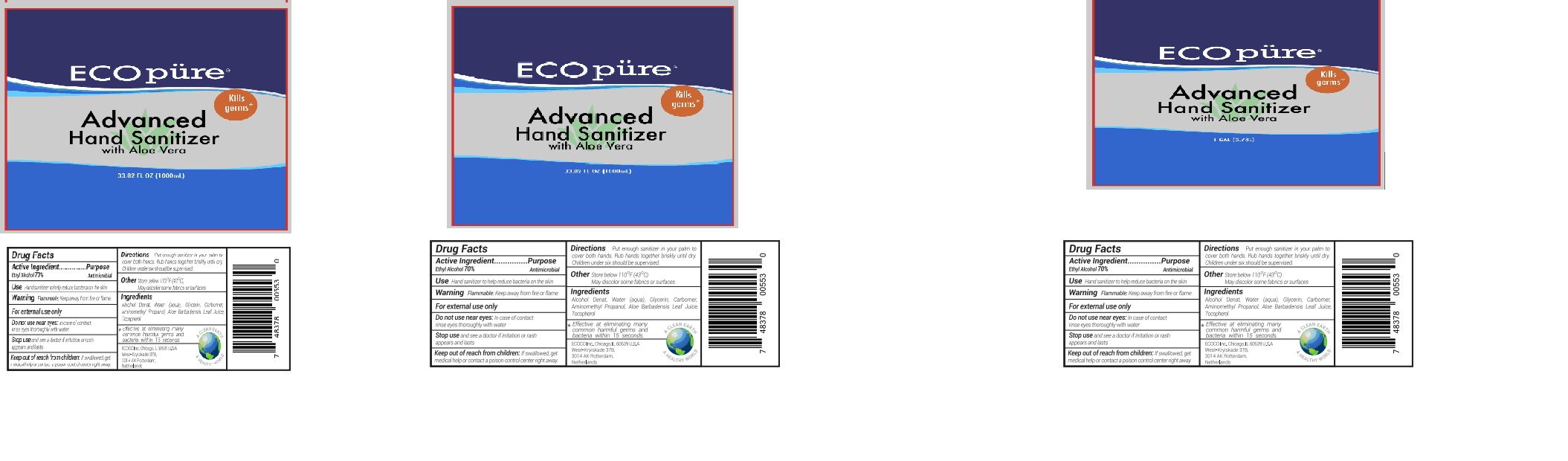 DRUG LABEL: Advanced Hand Sanitizer
NDC: 75541-005 | Form: LIQUID
Manufacturer: Ningbo Meiteli Cosmetic Co., Ltd.
Category: otc | Type: HUMAN OTC DRUG LABEL
Date: 20200430

ACTIVE INGREDIENTS: ALCOHOL 70 mL/100 mL
INACTIVE INGREDIENTS: GLYCERIN; CARBOMER 934; WATER; ALOE; AMINOMETHYLPROPANOL; TOCOPHEROL

Advanced Hand Sanitizer

Active Ingredient(s)

Ethyl Alcohol 70%

Purpose

Antimicrobial

Use

Hand Sanitizer to help reduce bacteria on the skin.

Warning

Flammable. Keep away from heat or flame

For external use only.

Do not use near eyes

In case of contact rinse eyes thoroughly with water.

Stop use

Stop use and see a doctor if imtation or rash appears and lasts

Keep out of reach of children. If swallowed, get medical help or contact a poison control Center right away.

Directions

Put enough sanitizer in your palm to cover both hands,Rub hands together brishly until dry,Children under six should be supervised

Other

- Store below 110F(43C)
- May discolor some fabrics or surfaces

Inactive ingredients

Alcohol Denat,Water(aqua),Glycerin,Carbomer,Aminomethylpropanol,Aloe Barbadensis Leaf Juice,Tocopherol